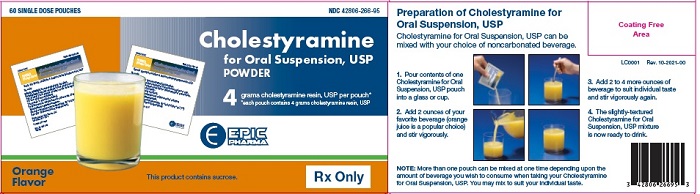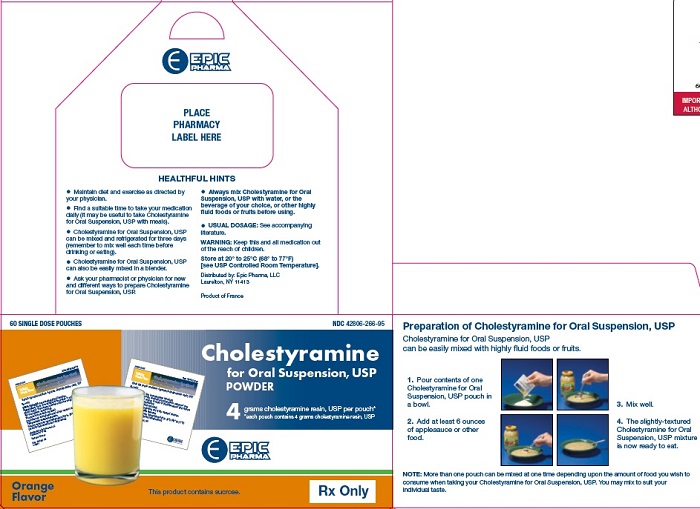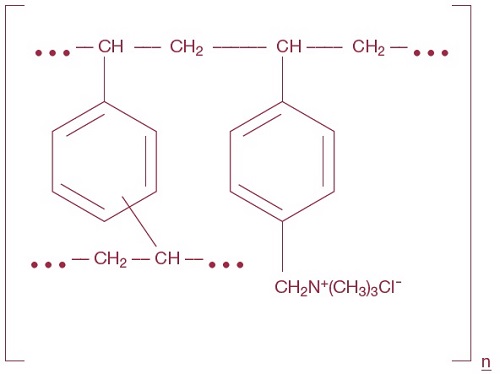 DRUG LABEL: CHOLESTYRAMINE
NDC: 42806-266 | Form: POWDER, FOR SUSPENSION
Manufacturer: EPIC PHARMA, LLC
Category: prescription | Type: HUMAN PRESCRIPTION DRUG LABEL
Date: 20251217

ACTIVE INGREDIENTS: CHOLESTYRAMINE 4 g/9 g
INACTIVE INGREDIENTS: ANHYDROUS CITRIC ACID; D&C YELLOW NO. 10; FD&C YELLOW NO. 6; FRUCTOSE; AMMONIUM GLYCYRRHIZATE; ORANGE; PECTIN; PROPYLENE GLYCOL ALGINATE; SORBITOL; SUCROSE; XANTHAN GUM

Cholestyramine for Oral Suspension, USP

DESCRIPTION

Cholestyramine for Oral Suspension, USP powder, the chloride salt of a basic anion exchange resin, a cholesterol lowering agent, is intended for oral administration. Cholestyramine resin is quite hydrophilic, but insoluble in water. Cholestyramine resin is not absorbed from the digestive tract. Each Nine grams of Cholestyramine for Oral Suspension, USP powder contain 4 grams of cholestyramine resin. It is represented by the following structural formula:

Representation of structure of main polymeric groups

Inactive ingredients: citric acid anhydrous, fructose, mono ammonium glycyrrhizinate, pectin, propylene glycol alginate, sorbitol, sucrose, xanthan gum, natural and artificial orange flavor, D&C yellow No. 10 aluminum lake, FD&C yellow No. 6 aluminum lake.

CLINICAL PHARMACOLOGY

Cholesterol is probably the sole precursor of bile acids. During normal digestion, bile acids are secreted into the intestines. A major portion of the bile acids is absorbed from the intestinal tract and returned to the liver via the enterohepatic circulation. Only very small amounts of bile acids are found in normal serum.

Cholestyramine resin adsorbs and combines with the bile acids in the intestine to form an insoluble complex which is excreted in the feces. This results in a partial removal of bile acids from the enterohepatic circulation by preventing their absorption.

The increased fecal loss of bile acids due to cholestyramine resin administration leads to an increased oxidation of cholesterol to bile acids, a decrease in beta lipoprotein or low density lipoprotein plasma levels and a decrease in serum cholesterol levels. Although in man, cholestyramine resin produces an increase in hepatic synthesis of cholesterol, plasma cholesterol levels fall.

In patients with partial biliary obstruction, the reduction of serum bile acid levels by cholestyramine resin reduces excess bile acids deposited in the dermal tissue with resultant decrease in pruritus.

Clinical Studies

In a large, placebo-controlled, multi-clinic study, LRC-CPPT^1, hypercholesterolemic subjects treated with cholestyramine resin had mean reduction in total and low-density lipoprotein cholesterol (LDL-C) which exceeded those for diet and placebo treatment by 7.2% and 10.4%, respectively. Over the seven-year study period the cholestyramine resin group experienced a 19% reduction (relative to the incidence in the placebo group) in the combined rate of coronary heart disease death plus non-fatal myocardial infarction (cumulative incidence of 7% cholestyramine resin and 8.6% placebo). The subjects included in the study were men aged 35 to 59 with serum cholesterol levels above 265 mg/dL and no previous history of heart disease. It is not clear to what extent these findings can be extrapolated to females and other segments of the hypercholesterolemic population. (see also PRECAUTIONS, Carcinogenesis, Mutagenesis, Impairment of Fertility).

Two controlled clinical trials have examined the effects of cholestyramine monotherapy upon coronary atherosclerotic lesions using coronary arteriography. In the NHLBI Type II Coronary Intervention Trial^2, 116 patients (80% male) with coronary artery disease (CAD) documented by arteriography were randomized to cholestyramine resin or placebo for five years of treatment. Final study arteriography revealed progression of coronary artery disease in 49% of placebo patients compared to 32% of the cholestyramine resin group (p<0.05).

In the St. Thomas Atherosclerosis Regression Study (STARS)^3, 90 hypercholesterolemic men with CAD were randomized to three blinded treatments: usual care, lipid-lowering diet and lipid-lowering diet plus cholestyramine resin. After 36 months, follow-up coronary arteriography revealed progression of disease in 46% of usual care patients, 15% of patients on lipid-lowering diet and 12% of those receiving diet plus cholestyramine resin (p<0.02). The mean absolute width of coronary segments decreased in the usual care group, increased slightly (0.003 mm) in the diet group and increased by 0.103 mm in the diet plus cholestyramine group (p<0.05). Thus in these randomized controlled clinical trials using coronary arteriography, cholestyramine resin monotherapy has been demonstrated to slow progression^2,3 and promote regression^3 of atherosclerotic lesions in the coronary arteries of patients with coronary artery disease.

The effect of intensive lipid-lowering therapy on coronary atherosclerosis has been assessed by arteriography in hyperlipidemic patients. In these randomized, controlled clinical trials, patients were treated for two to four years by either conventional measures (diet, placebo or in some cases low dose resin) or intensive combination therapy using diet plus colestipol (an anion exchange resin with a mechanism of action and an effect on serum lipids similar to that of Cholestyramine for Oral Suspension) plus either nicotinic acid or lovastatin. When compared to conventional measures, intensive lipid-lowering combination therapy significantly reduced the frequency of progression and increased the frequency of regression of coronary atherosclerotic lesions in patients with or at risk for coronary artery disease.

INDICATIONS AND USAGE

1) Cholestyramine for Oral Suspension, USP powder is indicated as adjunctive therapy to diet for the reduction of elevated serum cholesterol in patients with primary hypercholesterolemia (elevated low density lipoprotein [LDL] cholesterol) who do not respond adequately to diet. Cholestyramine for Oral Suspension, USP powder may be useful to lower LDL cholesterol in patients who also have hypertriglyceridemia, but it is not indicated where hypertriglyceridemia is the abnormality of most concern.

Therapy with lipid-altering agents should be a component of multiple risk factor intervention in those individuals at significantly increased risk for atherosclerotic vascular disease due to hypercholesterolemia. Treatment should begin and continue with dietary therapy specific for the type of hyperlipoproteinemia determined prior to initiation of drug therapy. Excess body weight may be an important factor and caloric restriction for weight normalization should be addressed prior to drug therapy in the overweight.

Prior to initiating therapy with cholestyramine resin, secondary causes of hypercholesterolemia (e.g., poorly controlled diabetes mellitus, hypothyroidism, nephrotic syndrome, dysproteinemias, obstructive liver disease, other drug therapy, alcoholism), should be excluded and a lipid profile performed to assess Total cholesterol, HDL-C and triglycerides (TG). For individuals with TG less than 400 mg/dL (<4.5 mmol/L), LDL-C can be estimated using the following equation:

LDL-C = Total cholesterol - [(TG/5) + HDL-C]

For TG levels > 400 mg/dL, this equation is less accurate and LDL-C concentrations should be determined by ultracentrifugation. In hypertriglyceridemic patients, LDL-C may be low or normal despite elevated Total-C. In such cases cholestyramine resin may not be indicated.

Serum cholesterol and triglyceride levels should be determined periodically based on NCEP guidelines to confirm initial and adequate long-term response. A favorable trend in cholesterol reduction should occur during the first month of cholestyramine resin therapy. The therapy should be continued to sustain cholesterol reduction. If adequate cholesterol reduction is not attained, increasing the dosage of cholestyramine resin or adding other lipid-lowering agents in combination with cholestyramine resin should be considered.

Since the goal of treatment is to lower LDL-C, the NCEP4 recommends that LDL-C levels be used to initiate and assess treatment response. If LDL-C levels are not available then Total-C alone may be used to monitor long-term therapy. A lipoprotein analysis (including LDL-C determination) should be carried out once a year. The NCEP treatment guidelines are summarized below.

Definite Atherosclerotic Disease* | Two or More Other Risk Factors† | LDL-Cholesterol mg/dL (mmol/L)
Definite Atherosclerotic Disease* | Two or More Other Risk Factors† | Initiation Level | Goal
No | No | ≥ 190 (≥ 4.9) | ≥ 60 (4.1)
No | Yes | ≥ 160 (≥ 4.1) | ≥ 130 (3.4)
Yes | Yes or No | ≥ 130 (≥ 3.4) | ≥ 100 (‑2.6)

*Coronary heart disease or peripheral vascular disease (including symptomatic carotid artery disease).

†Other risk factors for coronary heart disease (CHD) include: age (males 45 years; females: 55 years or premature menopause without estrogen replacement therapy); family history of premature CHD; current cigarette smoking; hypertension; confirmed HDL-C <35 mg/dL (<0.91 mmol/L); and diabetes mellitus. Subtract one risk factor if HDL-C is 60 mg/dL (1.6 mmol/L).

Cholestyramine resin monotherapy has been demonstrated to retard the rate of progression^2,3 and increase the rate of regression^3 of coronary atherosclerosis.

2) Cholestyramine for Oral Suspension, USP powder, is indicated for the relief of pruritus associated with partial biliary obstruction. Cholestyramine resin has been shown to have a variable effect on serum cholesterol in these patients. Patients with primary biliary cirrhosis may exhibit an elevated cholesterol as part of their disease.

CONTRAINDICATIONS

Cholestyramine for Oral Suspension, USP powder is contraindicated in patients with complete biliary obstruction where bile is not secreted into the intestine and in those individuals who have shown hypersensitivity to any of its components.

PRECAUTIONS

General

Chronic use of cholestyramine resin may be associated with increased bleeding tendency due to hypoprothrombinemia associated with Vitamin K deficiency. This will usually respond promptly to parenteral Vitamin K1 and recurrences can be prevented by oral administration of Vitamin K1. Reduction of serum or red cell folate has been reported over long term administration of cholestyramine resin. Supplementation with folic acid should be considered in these cases.

There is a possibility that prolonged use of cholestyramine resin, since it is a chloride form of anion exchange resin, may produce hyperchloremic acidosis. This would especially be true in younger and smaller patients where the relative dosage may be higher. Caution should also be exercised in patients with renal insufficiency or volume depletion and in patients receiving concomitant spironolactone.

Cholestyramine resin may produce or worsen preexisting constipation. The dosage should be increased gradually in patients to minimize the risk of developing fecal impaction. In patients with preexisting constipation, the starting dose should be 1 pouch or 1 scoop once daily for 5 to 7 days, increasing to twice daily with monitoring of constipation and of serum lipoproteins, at least twice, 4 to 6 weeks apart. Increased fluid intake and fiber intake should be encouraged to alleviate constipation and a stool softener may occasionally be indicated. If the initial dose is well tolerated, the dose may be increased as needed by one dose/day (at monthly intervals) with periodic monitoring of serum lipoproteins. If constipation worsens or the desired therapeutic response is not achieved at one to six doses/day, combination therapy or alternate therapy should be considered. Particular effort should be made to avoid constipation in patients with symptomatic coronary artery disease. Constipation associated with cholestyramine resin may aggravate hemorrhoids.

Information for Patients

Inform your physician if you are pregnant or plan to become pregnant or are breast-feeding. Drink plenty of fluids and mix each 9 gram dose of Cholestyramine for Oral Suspension USP powder in at least 2 to 6 ounces of fluid before taking. Sipping or holding the resin suspension in the mouth for prolonged periods may lead to changes in the surface of the teeth resulting in discoloration, erosion of enamel or decay; good oral hygiene should be maintained.

Laboratory Tests

Serum cholesterol levels should be determined frequently during the first few months of therapy and periodically thereafter. Serum triglyceride levels should be measured periodically to detect whether significant changes have occurred.

The LRC-CPPT showed a dose-related increase in serum triglycerides of 10.7% to 17.1% in the cholestyramine-treated group, compared with an increase of 7.9% to 11.7% in the placebo group. Based on the mean values and adjusting for the placebo group, the cholestyramine-treated group showed an increase of 5% over pre-entry levels the first year of the study and an increase of 4.3% the seventh year.

Drug Interactions

Cholestyramine resin may delay or reduce the absorption of concomitant oral medication such as phenylbutazone, warfarin, thiazide diuretics (acidic) or propranolol (basic), as well as tetracycline, penicillin G, phenobarbital, thyroid and thyroxine preparations, estrogens and progestins and digitalis. Interference with the absorption of oral phosphate supplements has been observed with another positivelycharged bile acid sequestrant. Cholestyramine resin may interfere with the pharmacokinetics of drugs that undergo enterohepatic circulation. The discontinuance of cholestyramine resin could pose a hazard to health if a potentially toxic drug such as digitalis has been titrated to a maintenance level while the patient was taking cholestyramine resin.

Because cholestyramine binds bile acids, cholestyramine resin may interfere with normal fat digestion and absorption and thus may prevent absorption of fat soluble vitamins such as A, D, E and K. When cholestyramine resin is given for long periods of time, concomitant supplementation with water-miscible (or parenteral) forms of fat soluble vitamins should be considered.

SINCE CHOLESTYRAMINE RESIN MAY BIND OTHER DRUGS GIVEN CONCURRENTLY, IT IS RECOMMENDED THAT PATIENTS TAKE OTHER DRUGS AT LEAST 1 HOUR BEFORE OR 4 TO 6 HOURS AFTER CHOLESTYRAMINE RESIN (OR AT AS GREAT AN INTERVAL AS POSSIBLE) TO AVOID IMPEDING THEIR ABSORPTION.

Carcinogenesis, Mutagenesis, Impairment of Fertility

In studies conducted in rats in which cholestyramine resin was used as a tool to investigate the role of various intestinal factors, such as fat, bile salts and microbial flora, in the development of intestinal tumors induced by potent carcinogens, the incidence of such tumors was observed to be greater in cholestyramine resin-treated rats than in control rats.

The relevance of this laboratory observation from studies in rats to the clinical use of cholestyramine resin is not known. In the LRCCPPT study referred to above, the total incidence of fatal and nonfatal neoplasms was similar in both treatment groups. When the many different categories of tumors are examined, various alimentary system cancers were somewhat more prevalent in the cholestyramine group. The small numbers and the multiple categories prevent conclusions from being drawn. However, in view of the fact that cholestyramine resin is confined to the GI tract and not absorbed and in light of the animal experiments referred to above, a six-year post-trial follow-up of the LRC-CPPT5 patient population has been completed (a total of 13.4 years of in-trial plus post-trial follow-up) and revealed no significant difference in the incidence of cause-specific mortality or cancer morbidity between cholestyramine and placebo treated patients.

Pregnancy

Pregnancy Category C

There are no adequate and well controlled studies in pregnant women. The use of cholestyramine in pregnancy or lactation or by women of childbearing age requires that the potential benefits of drug therapy be weighted against the possible hazards to the mother and child. Cholestyramine is not absorbed systemically, however, it is known to interfere with absorption of fat-soluble vitamins; accordingly, regular prenatal supplementation may not be adequate (see PRECAUTIONS, Drug Interactions).

Nursing Mothers

Caution should be exercised when cholestyramine resin is administered to a nursing mother. The possible lack of proper vitamin absorption described in the “Pregnancy” section may have an effect on nursing infants.

Pediatric Use

Although an optimal dosage schedule has not been established, standard texts(^6,7) list a usual pediatric dose of 240 mg/kg/day of anhydrous cholestyramine resin in two to three divided doses, normally not to exceed 8 g/day with dose titration based on response and tolerance.

In calculating pediatric dosages, 44.4 mg of anhydrous cholestyramine resin are contained in 100 mg of Cholestyramine for Oral Suspension USP.

The effects of long-term drug administration, as well as its effect in maintaining lowered cholesterol levels in pediatric patients, are unknown. Also see ADVERSE REACTIONS.

ADVERSE REACTIONS

The most common adverse reaction is constipation. When used as a cholesterol-lowering agent predisposing factors for most complaints of constipation are high dose and increased age (more than 60 years old). Most instances of constipation are mild, transient and controlled with conventional therapy. Some patients require a temporary decrease in dosage or discontinuation of therapy.

Less Frequent Adverse Reactions - Abdominal discomfort and/or pain, flatulence, nausea, vomiting, diarrhea, eructation, anorexia, steatorrhea, bleeding tendencies due to hypoprothrombinemia (Vitamin K deficiency) as well as Vitamin A (one case of night blindness reported) and D deficiencies, hyperchloremic acidosis in children, osteoporosis, rash and irritation of the skin, tongue and perianal area. Rare reports of intestinal obstruction, including two deaths, have been reported in pediatric patients.

Occasional calcified material has been observed in the biliary tree, including calcification of the gallbladder, in patients to whom cholestyramine resin has been given. However, this may be a manifestation of the liver disease and not drug related.

One patient experienced biliary colic on each of three occasions on which he took a cholestyramine for oral suspension product. One patient diagnosed as acute abdominal symptom complex was found to have a “pasty mass” in the transverse colon on x-ray.

Other events (not necessarily drug related) reported in patients taking cholestyramine resin include:

OVERDOSAGE

Overdosage of cholestyramine resin has been reported in a patient taking 150% of the maximum recommended daily dosage for a period of several weeks. No ill effects were reported. Should an overdosage occur, the chief potential harm would be obstruction of the gastrointestinal tract. The location of such potential obstruction, the degree of obstruction and the presence or absence of normal gut motility would determine treatment.

DOSAGE AND ADMINISTRATION

The recommended starting adult dose for Cholestyramine for Oral Suspension, USP powder is 1 pouch or 1 level scoopful (9 grams of Cholestyramine for Oral Suspension, USP powder contains 4 grams of anhydrous cholestyramine resin) once or twice a day. The recommended maintenance dose for Cholestyramine for Oral Suspension, USP powder is 2 to 4 pouches or scoopfuls daily (8 to 16 grams anhydrous cholestyramine resin) divided into two doses. It is recommended that increases in dose be gradual with periodic assessment of lipid/lipoprotein levels at intervals of not less than 4 weeks. The maximum recommended daily dose is 6 pouches or scoopfuls of Cholestyramine for Oral Suspension, USP powder (24 grams of anhydrous cholestyramine resin). The suggested time of administration is at mealtime but may be modified to avoid interference with absorption of other medications. Although the recommended dosing schedule is twice daily, Cholestyramine for Oral Suspension, USP powder may be administered in 1 to 6 doses per day.

Cholestyramine for Oral Suspension, USP powder should not be taken in its dry form. Always mix the dry powder with water or other fluids before ingesting. See Preparation Instructions.

Concomitant Therapy

Preliminary evidence suggests that the lipid-lowering effects of cholestyramine on total and LDL-cholesterol are enhanced when combined with a HMG-COA reductase inhibitor, e.g., pravastatin, lovastatin, simvastatin and fluvastatin. Additive effects on LDL-cholesterol are also seen with combined nicotinic acid/cholestyramine therapy. See PRECAUTIONS, Drug Interactions for recommendations on administering concomitant therapy.

Preparation

The color of Cholestyramine for Oral Suspension, USP powder may vary somewhat from batch to batch but this variation does not affect the performance of the product. Place the contents of one single-dose pouch or one level scoopful of Cholestyramine for Oral Suspension, USP powder in a glass or cup. Add at least 2 to 3 ounces of water or the beverage of your choice. Stir to a uniform consistency.

Cholestyramine for Oral Suspension, USP powder may also be mixed with highly fluid soups or pulpy fruits with a high moisture content such as applesauce or crushed pineapple.

HOW SUPPLIED

Cholestyramine for Oral Suspension, USP powder orange flavor is available in cartons of sixty 9 gram pouches and in cans containing 378 grams. Nine grams of Cholestyramine for Oral Suspension, USP powder, contains 4 grams of anhydrous cholestyramine resin.

NDC # 42806-266-95 Carton of 60 pouches

NDC # 42806-267-97 Can, 378 g (containing a scoop that is not interchangeable with scoops from other products)

Storage

Store at 20° to 25°C (68° to 77°F) [see USP Controlled Room Temperature].

Always replace plastic lid after using.

KEEP OUT OF THE REACH OF CHILDREN.

References

1. The Lipid Research Clinics Coronary Primary Prevention Trial Results: (I) Reduction in Incidence of Coronary Heart Disease; (II) The Relationship of Reduction in Incidence of Coronary Heart Disease to Cholesterol Lowering. JAMA. 1984; 251:351-374.
2. Brensike JF, Levy RI, Kelsey SF, et al. Effects of therapy with cholestyramine on progression of coronary arteriosclerosis: results of the NHLBI type II coronary intervention study. Circulation 1984; 69:313-24.
3. Watts, GF, Lewis B, Brunt JNH, Lewis ES, et al. Effects on coronary artery disease of lipid-lowering diet or diet plus cholestyramine, in the St. Thomas Atherosclerosis Regression Study (STARS). Lancet 1992; 339:563-69.
4. National Cholesterol Education Program. Second Report of the Expert panel on Detection, Evaluation and Treatment of High Blood Cholesterol in Adults (Adult Treatment Panel II). Circulation 1994 Mar;89 (3):1333-445.
5. The Lipid Research Clinics Investigators. The Lipid Research Clinics Coronary Primary Prevention Trial: Results of 6 Years of Post-Trial Follow-up. Arch Intern Med 1992; 152:1399-1410.
6. Behrman RE et al (eds): Nelson, Textbook of Pediatrics, ed 15. Philadelphia, PA, WB Saunders Company, 1996.
7. Takemoto CK et al (eds): Pediatric Dosage Handbook, ed 3. Cleveland/Akron, OH, Lexi-Comp, Inc., 1996/1997.

To report SUSPECTED ADVERSE REACTIONS, contact Epic pharma LLC at 1-888-374-2791 or FDA at 1-800-FDA-1088 or www.fda.gov/medwatch.

Distributed by

Epic Pharma LLC

Laurelton, NY 11413

OS0002

Rev. 02-2025-00

MF266REV02/25